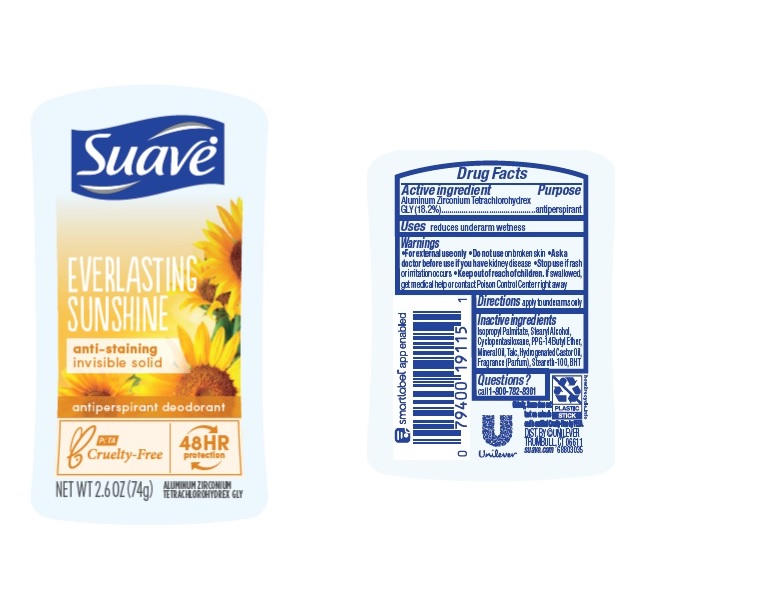 DRUG LABEL: Suave
NDC: 64942-1991 | Form: STICK
Manufacturer: Conopco Inc. d/b/a/ Unilever
Category: otc | Type: HUMAN OTC DRUG LABEL
Date: 20221207

ACTIVE INGREDIENTS: ALUMINUM ZIRCONIUM TETRACHLOROHYDREX GLY 18.2 g/100 g
INACTIVE INGREDIENTS: TALC; STEARETH-100; HYDROGENATED CASTOR OIL; ISOPROPYL PALMITATE; PPG-14 BUTYL ETHER; CYCLOMETHICONE 5; BUTYLATED HYDROXYTOLUENE; STEARYL ALCOHOL; MINERAL OIL

Suave Everlasting Sunshine 48HR Protection Antiperspirant Deodorant

Drug Facts

Active ingredient

Aluminum Zirconium Tetrachlorohydrex GLY (18.2 %)

Purpose

antiperspirant

Uses

reduces underarm wetness

Warnings

• For externaluse only.
• Do not use on broken skin .
• Ask a doctor before use if you have kidney disease.
• Stop use if rash or irritation occurs.

• Keep out of reach of children.

If swallowed, get medical help or contact a Poison Control Center right away.

Directions

apply to underarms only

Inactive ingredients

Isopropyl Palmitate, Stearyl Alcohol, Cyclopentasiloxane, PPG-14 Butyl Ether, Mineral Oil, Talc, Hydrogenated Castor Oil, Fragrance (Parfum), Steareth-100, BHT

Questions?

Call 1-800-782-8301